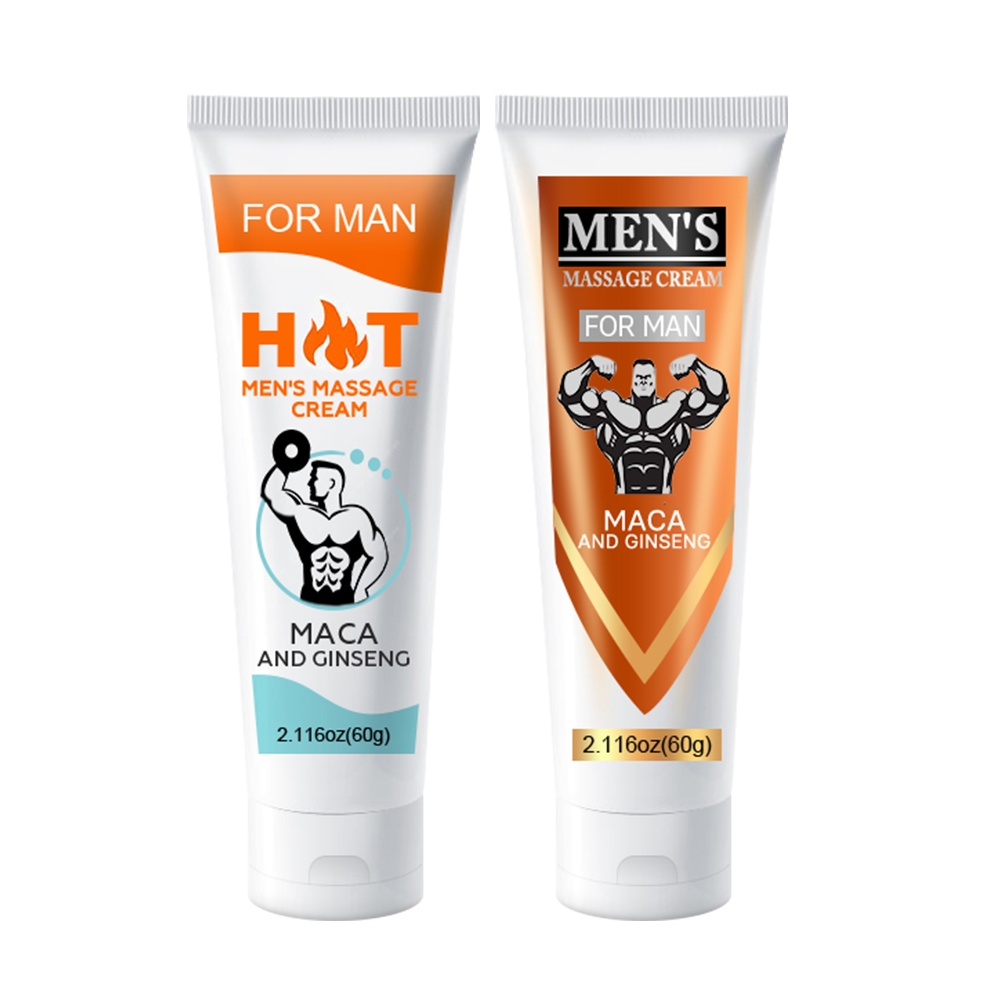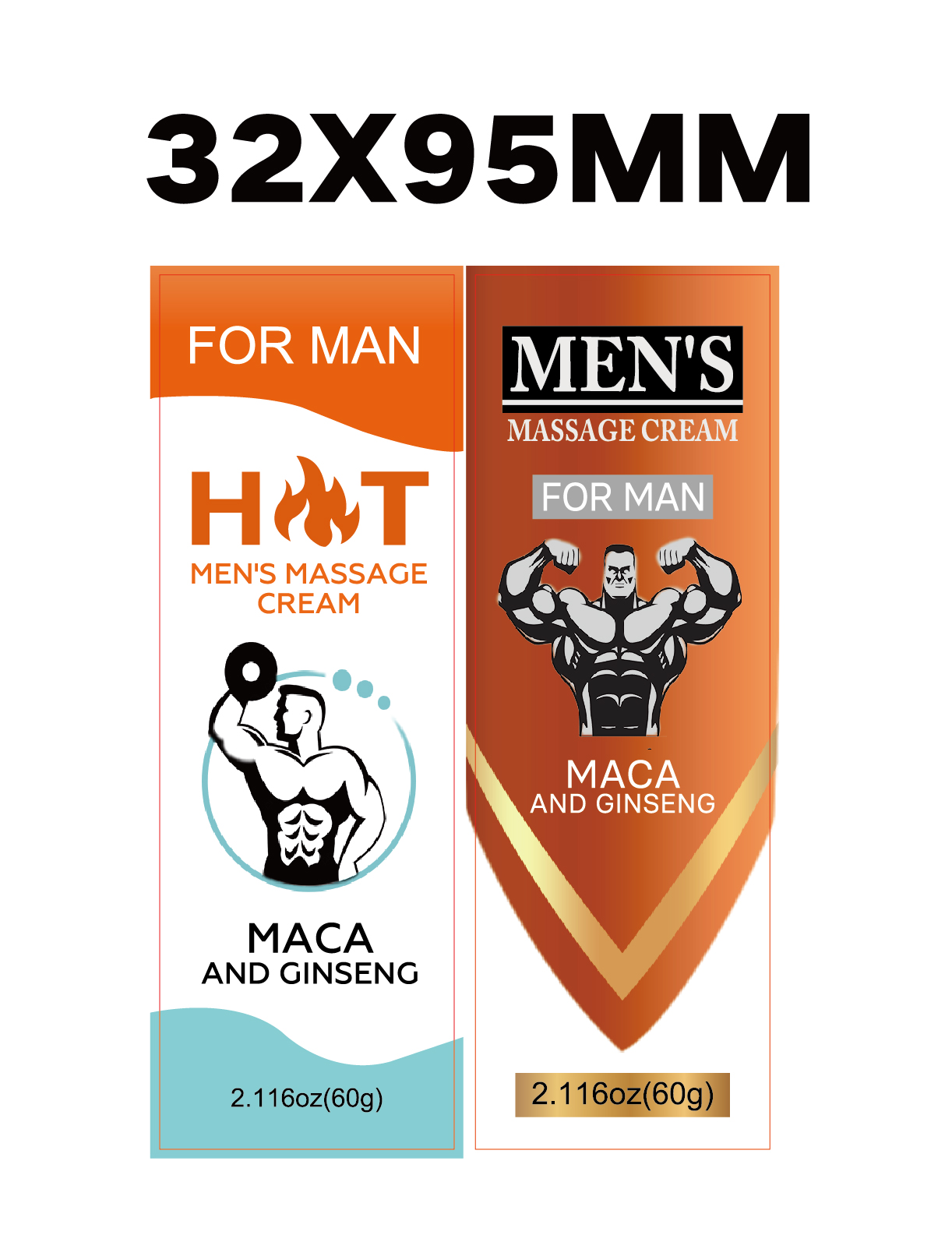 DRUG LABEL: mens massage cream
NDC: 84025-272 | Form: CREAM
Manufacturer: Guangzhou Yanxi Biotechnology Co., Ltd
Category: otc | Type: HUMAN OTC DRUG LABEL
Date: 20241126

ACTIVE INGREDIENTS: NIACINAMIDE 3 mg/60 g; ALLANTOIN 2 mg/60 g
INACTIVE INGREDIENTS: WATER

DOSAGE AND ADMINISTRATION

Clean The Private Parts, Squeeze Out The Right Amount Of Cream And Smear The Required Parts.

WARNINGS

Keep out of children

INACTIVE INGREDIENT

Aqua

INDICATIONS AND USAGE

For daily body care

Keep out of children

PURPOSE

Men’s energy strength massage spary god of war seven times a night.